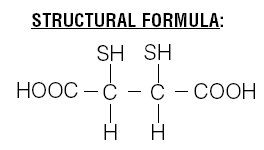 DRUG LABEL: Unknown
Manufacturer: GE Healthcare
Category: prescription | Type: HUMAN PRESCRIPTION DRUG LABELING
Date: 20070803

DMSA
Kit for the Preparation of Technetium Tc99m Succimer Injection

Rx ONLY

DIAGNOSTIC - FOR INTRAVENOUS USE

DESCRIPTION

Each vial contains a sterile, pyrogen-free freeze-dried mixture of 1.0 mg dimercaptosuccinic acid, 0.42 mg stannous chloride dihydrate [0.38 mg (minimum) stannous chloride dihydrate (SnCl2•2H2O) and 0.46 mg (maximum) total tin expressed as stannous chloride dihydrate (SnCl2•2H2O)], 0.70 mg ascorbic acid, and 50.0 mg inositol. After freeze-drying, vials are sealed under a nitrogen atmosphere with a rubber closure. Sodium hydroxide and hydrochloric acid have been used for pH adjustment. When sterile, oxidant-free, pyrogen-free sodium pertechnetate Tc99m injection in isotonic saline is combined with the vial contents, following the instructions provided with the kit, a complex is formed. After 10 minutes incubation the reconstituted solution is ready for intravenous injection.

Chemical Name: meso-2,3-dimercaptosuccinic acid

The succimer component of DMSA consists of more than 90% meso isomer and less than 10% d,l isomer.

PHYSICAL CHARACTERISTICS

Technetium Tc99m decays by isomeric transition with a physical half-life of 6.02 hours [Kocher, David C., "Radioactive Decay Data Tables," DOE/TIC-11026,108 (1981).] . The principal photon that is useful for detection and imaging studies is listed in Table 1.

Table 1. Principal Radiation Emission Data
Radiation | Mean % / Disintegration | Mean Energy (keV)
Gamma 2 | 89.07 | 140.5

EXTERNAL RADIATION

The specific gamma ray constant for technetium Tc99m is 0.78 R/hr-mCi at 1 cm. The first half value layer is 0.017 cm of Pb. To facilitate control of the radiation exposure from millicurie amounts of this radionuclide, the use of a 0.25 cm thickness of Pb will attenuate the radiation emitted by a factor of about 1,000.

Table 2. Radiation Attenuation by Lead Shielding
Shield Thickness (Pb) cm | Coefficient of Attenuation
0.02 | 0.5
0.08 | 0.1
0.16 | 0.01
0.25 | 0.001
0.33 | 0.0001

To correct for physical decay of this radionuclide, the fractions that remain at selected intervals after the time of calibration are shown in Table 3.

Table 3. Physical Decay Chart: Tc99m, half-life 6.02 hours
Hours | Fraction Remaining | Hours | Fraction Remaining
0 [Calibration Time] | 1.000 | 7 | 0.447
1 | 0.891 | 8 | 0.398
2 | 0.794 | 9 | 0.355
3 | 0.708 | 10 | 0.316
4 | 0.631 | 11 | 0.282
5 | 0.562 | 12 | 0.251
6 | 0.501

CLINICAL PHARMACOLOGY

After intravenous administration, technetium Tc99m succimer injection is distributed in the plasma, apparently bound to plasma proteins. There is negligible activity in the red blood cells. The activity is cleared from the plasma with a half-time of about 60 minutes and concentrates in the renal cortex. Approximately 16% of the activity is excreted in the urine within two hours. At six hours about 20% of the dose is concentrated in each kidney.

INDICATIONS AND USAGE

DMSA is to be used as an aid in the scintigraphic evaluation of renal parenchymal disorders.

CONTRAINDICATIONS

None known.

WARNINGS

None.

PRECAUTIONS

General

As in the use of any radioactive material, care should be taken to minimize radiation exposure to the patient consistent with proper patient management and to ensure minimum radiation exposure to occupational workers.

DMSA should be used between 10 minutes and 4 hours following reconstitution (see "Preparation" section). Any unused portion should be discarded after that time.

Some patients with advanced renal failure may exhibit poor renal intake of Tc99m DMSA. It has been reported that satisfactory images may be obtained in some of these patients by delaying imaging for up to 24 hours.

The contents of the kit vials are intended only for use in the preparation of DMSA Injection and are not to be directly administered to the patient.

The contents of the kit vials are not radioactive. However, after Tc99m is added, adequate shielding of the final preparation must be maintained.

Radiopharmaceuticals should be used only by physicians who are qualified by training and experience in the safe use and handling of radionuclides and whose experience and training have been approved by the appropriate government agency authorized to license the use of radionuclides.

Carcinogenesis, Mutagenesis, Impairment of Fertility

No long term animal studies have been performed to evaluate carcinogenic potential, mutagenic potential, or whether technetium Tc99m succimer injection affects fertility in males or females.

Pregnancy Category C

Animal reproduction studies have not been conducted with technetium Tc99m succimer injection. It is also not known whether technetium Tc99m succimer injection can cause fetal harm when administered to a pregnant woman or can affect reproduction capacity. Technetium Tc99m succimer injection should be administered to a pregnant woman only if clearly needed.

Ideally, examinations using radiopharmaceuticals, especially those elective in nature, of a woman of child bearing capability should be performed during the first few (approximately 10) days following the onset of menses.

Nursing Mothers

Technetium Tc99m is excreted in human milk during lactation; therefore, formula feedings should be substituted for breast feedings.

Pediatric Use

Safety and effectiveness in pedriatric patients have not been established

Geriatric Use

Clinical studies of DMSA did not include sufficient numbers of subjects age 65 and over to determine whether they respond differently from younger patients. Other reported clinical experience has not identified differences in responses between the elderly and younger patients. In general, dose selection for an elderly patient should be cautious usually starting at the low end of the dosing range, reflecting the greater frequency of decreased hepatic, renal or cardiac function, and of concomitant disease or other drug therapy.

This drug is known to be substantially excreted by the kidney, and the risk of toxic reactions to this drug may be greater in patients with impaired renal function. Because elderly patients are more likely to have decreased renal function, care should be taken in dose selection, and it may be useful to monitor renal function.

ADVERSE REACTIONS

Rare instances of syncope, fever, nausea and maculopapular skin rash have been reported.

DOSAGE AND ADMINISTRATION

The suggested dose range for slow I.V. administration to be employed in the average patient (70 kg) for renal parenchymal imaging is 74-222 MBq, 2-6 mCi technetium Tc99m succimer injection.

The product must be used between 10 minutes to 4 hours following preparation (see "Preparation" section). Acceptable renal images may be obtained beginning 1 to 2 hours post injection. Any unused portion should be discarded after that time.

The patient dose should be measured by a suitable radioactivity calibration system immediately prior to administration.

Do not use after the expiration date stated on the label. The components of the kit are supplied sterile and pyrogen-free. Aseptic procedures normally employed in making additions and withdrawals from sterile, pyrogen-free containers should be used during addition of sodium pertechnetate Tc99m injection solutions and during the withdrawal of doses for patient administration.

Parenteral drug products should be inspected visually for particulate matter and discoloration prior to administration.

RADIATION DOSIMETRY

The estimated absorbed radiation doses [Method of Calculation: A schema for Absorbed-Dose Calculations for Biologically Distributed Radionuclides, Supplement No. 1, MIRD Pamphlet No. 1, J. Nucl. Med., p. 7, 1968.] , [Biological Data: Arnold, R.W; Subramanian, G.; McAfee, J.G.; Blair, R.J.; Thomas, F.D.; Comparison of Tc99m complexes for renal imaging, J. Nucl. Med., 16, pp. 357-367, 1975.] to an average adult (70 kg) are shown in Table 4.

Table 4. Absorbed Radiation Dose
Tissue | mGy / 222 MBq | rads / 6 mCi
Bladder Wall | 4.2 | 0.42
Kidneys (total) | 37.8 | 3.78
Renal Cortices | 51.0 | 5.10
Liver | 1.9 | 0.19
Bone Marrow | 1.3 | 0.13
Ovaries | 0.8 | 0.08
Testes | 0.4 | 0.04
Total Body | 0.9 | 0.09

HOW SUPPLIED

Kit Contents

5 Vials containing a freeze-dried mixture of 1.0 mg dimercaptosuccinic acid, 0.42 mg stannous chloride dihydrate [0.38 mg (minimum) stannous chloride dihydrate (SnCl2•2H2O) and 0.46 mg (maximum) total tin expressed as stannous chloride dihydrate (SnCl2•2H2O)], 0.70 mg ascorbic acid, and 50.0 mg inositol.
5 Labels
1 Package Insert

NDC 017156-525-01

Storage

Store the kit at 2°-8°C (36°-46°F) and protect from light.

Preparation

The following directions must be carefully followed for optimum preparation of technetium Tc99m succimer injection:

Note: Use aseptic procedures throughout and take precautions to minimize radiation exposure by the use of suitable shielding. Waterproof gloves should be worn during the preparation procedure.

1. Place one of the vials in a suitable shielding container and swab the closure with a bacteriostatic swab.
2. Using a 10 mL sterile syringe, inject an appropriate amount (see notes 1 and 2) of the eluate from a Tc99m generator into the shielded vial. Before removing the syringe from the vial withdraw an equivalent volume of nitrogen from the space above the solution to normalize the pressure in the vial.
3. Carefully invert the vial a few times until the powder is completely dissolved.
4. Assay the total activity, complete the label provided and attach to the vial.
5. Incubate the vial for at least 10 minutes at room temperature.
6. Use the preparation between 10 minutes and 4 hours following reconstitution.

Note:

1. Not more than 1.48 GBq, 40 mCi technetium-99m in a volume of 1-6 mL should be added to the vial.
2. Before reconstitution, the eluate may be adjusted to the correct radioactive concentration by dilution with preservative-free, non-bacteriostatic saline for injection.
3. The use of technetium-99m solution complying with the specifications prescribed by the USP Monograph on Sodium Pertechnetate (99mTc) injection will yield a preparation of an appropriate quality.
4. It is recommended that with proper shielding and equipment, the final formulation be tested for radiochemical purity. If radiochemical purity is not adequate, discard the finished drug.

DISPOSAL

Any unused portion of the Tc99m-labeled kit must be stored and disposed of in accordance with the conditions of NRC radioactive materials license pursuant to 10 CFR Parts 20 and 35 or equivalent conditions pursuant to Agreement state regulation, or other regulatory agency authorized to license the use of radionuclides.

The unlabeled residual materials may be discarded in ordinary trash, provided that the vials and syringes read background with an appropriate low-range survey meter. It is suggested that all identification labels be destroyed before discarding.

This reagent kit is approved for use by persons licensed by the Illinois Emergency Management Agency pursuant to 32 Ill. Code Adm. Section, Section 330.260(a) and 335.4010 or under equivalent licenses of the U.S. Nuclear Regulatory Commission, or an Agreement State.

Manufactured for:
GE Healthcare
Medi-Physics, Inc.
3350 North Ridge Avenue
Arlington Heights, IL 60004
1-800-633-4123 (Toll Free)

By:
GE Healthcare Ltd.
Little Chalfont, HP7 9NA, UK

GE and the GE Monogram are trademarks of General Electric Company.

43-4349H
L/2331/04

Revised February 2006